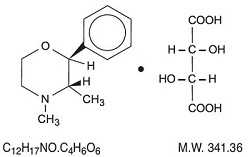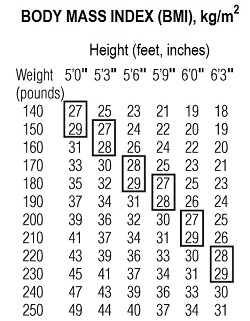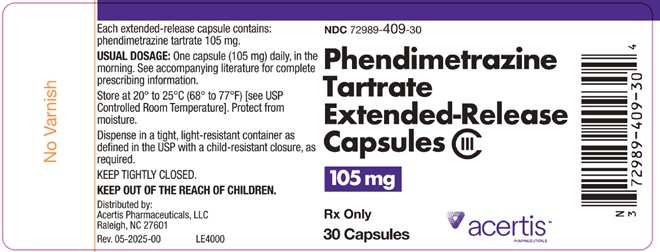 DRUG LABEL: PHENDIMETRAZINE TARTRATE
NDC: 72989-409 | Form: CAPSULE, EXTENDED RELEASE
Manufacturer: Acertis Pharmaceuticals, LLC
Category: prescription | Type: HUMAN PRESCRIPTION DRUG LABEL
Date: 20251219
DEA Schedule: CIII

ACTIVE INGREDIENTS: PHENDIMETRAZINE TARTRATE 105 mg/1 1
INACTIVE INGREDIENTS: FD&C BLUE NO. 1; FD&C RED NO. 40; GELATIN, UNSPECIFIED; POVIDONE, UNSPECIFIED; SILICON DIOXIDE; SODIUM LAURYL SULFATE; STARCH, CORN; SUCROSE; TALC; SHELLAC

Phendimetrazine Tartrate Extended-Release Capsules CIII

DESCRIPTION

Phendimetrazine tartrate, as the dextro isomer, has the chemical name of (2S,3S)-3,4-dimethyl-2-phenylmorpholine L-(+)-tartrate (1:1).

The structural formula is as follows:

Phendimetrazine tartrate is a white, odorless crystalline powder.

It is freely soluble in water; sparingly soluble in warm alcohol, insoluble in chloroform, acetone, ether and benzene. Each capsule, for oral administration, contains 105 mg phendimetrazine tartrate manufactured in a special base designed for prolonged release.

Inactive ingredients: FD&C Blue No. 1, FD&C Red No. 40, gelatin, pharmaceutical glaze, povidone, silica gel, sodium lauryl sulfate, corn starch, sucrose, talc and trace amounts of red imprinting ink.

CLINICAL PHARMACOLOGY

Phendimetrazine tartrate is a phenylalkylamine sympathomimetic amine with pharmacological activity similar to the prototype drugs of this class used in obesity, the amphetamines. Actions include central nervous system stimulation and elevation of blood pressure. Tachyphylaxis and tolerance have been demonstrated with all drugs of this class in which these phenomena have been looked for.

Drugs of this class used in obesity are commonly known as “anorectics” or “anorexigenics”. It has not been established, however, that the action of such drugs in treating obesity is primarily one of appetite suppression. Other central nervous system actions or metabolic effects, may be involved, for example. Adult obese subjects instructed in dietary management and treated with anorectic drugs, lose more weight on the average than those treated with placebo and diet, as determined in relatively short term clinical trials.

The magnitude of increased weight loss of drug-treated patients over placebo-treated patients is only a fraction of a pound a week. The rate of weight loss is greatest in the first weeks of therapy for both drug and placebo subjects and tends to decrease in succeeding weeks. The possible origins of the increased weight loss due to the various drug effects are not established. The amount of weight loss associated with the use of an anorectic drug varies from trial to trial, and the increased weight loss appears to be related in part to variables other than the drug prescribed, such as the physician investigator, the population treated, and the diet prescribed. Studies do not permit conclusions as to the relative importance of the drug and non-drug factors on weight loss.

The natural history of obesity is measured in years, whereas the studies cited are restricted to a few weeks duration, thus, the total impact of drug-induced weight loss over that of diet alone must be considered clinically limited.

The active drug, 105 mg of phendimetrazine tartrate in each capsule of this special extended-release dosage form approximates the action of three 35 mg immediate release doses taken at four hour intervals.

The major route of elimination is via the kidneys where most of the drug and metabolites are excreted. Some of the drug is metabolized to phenmetrazine and also phendimetrazine-N-oxide.

The average half-life of elimination when studied under controlled conditions is about 3.7 hours for both the extended-release and immediate release forms. The absorption half-life of the drug from the immediate release 35 mg phendimetrazine tablets is appreciably more rapid than the absorption rate of the drug from the extended-release formulation.

INDICATIONS AND USAGE

Phendimetrazine tartrate extended-release capsules are indicated in the management of exogenous obesity as a short term adjunct (a few weeks) in a regimen of weight reduction based on caloric restriction in patients with an initial body mass index (BMI) of greater than or equal to 30 kg/m^2 or greater than or equal to 27 kg/m^2 in the presence of other risk factors (e.g., controlled hypertension, diabetes, hyperlipidemia) who have not responded to appropriate weight reducing regimen (diet and/or exercise) alone.

Below is a chart of Body Mass Index (BMI) based on various heights and weights. BMI is calculated by taking the patient’s weight, in kilograms (kg), divided by the patient’s height, in meters (m), squared. Metric conversions are as follows: pounds ÷ 2.2 = kg; inches × 0.0254 = meters

The usefulness of agents of this class (see CLINICAL PHARMACOLOGY) should be measured against possible risk factors inherent in their use such as those described below. Phendimetrazine tartrate is indicated for use as monotherapy only.

CONTRAINDICATIONS

- History of cardiovascular disease (e.g., coronary artery disease, stroke, arrhythmias, congestive heart failure, uncontrolled hypertension, pulmonary hypertension)
- During or within 14 days following the administration of monoamine oxidase inhibitors
- Hyperthyroidism
- Glaucoma
- Agitated states
- History of drug abuse
- Pregnancy (see PRECAUTIONS, Pregnancy)
- Nursing
- Use in combination with other anorectic agents or CNS stimulants
- Known hypersensitivity or idiosyncratic reactions to sympathomimetics

WARNINGS

Phendimetrazine tartrate should not be used in combination with other anorectic agents, including prescribed drugs, over-the-counter preparations and herbal products.

In a case-control epidemiological study, the use of anorectic agents, including phendimetrazine tartrate, was associated with an increased risk of developing pulmonary hypertension, a rare, but often fatal disorder. The use of anorectic agents for longer than three months was associated with a 23-fold increase in the risk of developing pulmonary hypertension. Increased risk of pulmonary hypertension with repeated courses of therapy cannot be excluded.

The onset or aggravation of exertional dyspnea, or unexplained symptoms of angina pectoris, syncope, or lower extremity edema suggest the possibility of occurrence of pulmonary hypertension. Under these circumstances, phendimetrazine tartrate should be immediately discontinued, and the patient should be evaluated for the possible presence of pulmonary hypertension.

Valvular heart disease associated with the use of some anorectic agents such as fenfluramine and dexfenfluramine has been reported. Possible contributing factors include use for extended periods of time, higher than recommended dose, and/or use in combination with other anorectic drugs.

The potential risk of possible serious adverse effects such as valvular heart disease and pulmonary hypertension should be assessed carefully against the potential benefit of weight loss. Baseline cardiac evaluation should be considered to detect preexisting valvular heart diseases or pulmonary hypertension prior to initiation of phendimetrazine treatment. Phendimetrazine tartrate is not recommended in patients with known heart murmur or valvular heart disease. Echocardiogram during and after treatment could be useful for detecting any valvular disorders which may occur. Tolerance to the anorectic effect of phendimetrazine develops within a few weeks. When this occurs, its use should be discontinued; the maximum recommended dose should not be exceeded. Use of phendimetrazine tartrate within 14 days following the administration of monoamine oxidase inhibitors may result in a hypertensive crisis. Abrupt cessation of administration following prolonged high dosage results in extreme fatigue and depression. Because of the effect on the central nervous system, phendimetrazine may impair the ability of the patient to engage in potentially hazardous activities such as operating machinery or driving a motor vehicle; the patient should therefore be cautioned accordingly.

Phendimetrazine tartrate is not recommended for patients who used any anorectic agents within the prior year.

PRECAUTIONS

General

Caution is to be exercised in prescribing phendimetrazine tartrate for patients with even mild hypertension.

Insulin or oral hypoglycemic medication requirements in diabetes mellitus may be altered in association with the use of phendimetrazine and the concomitant dietary regimen.

Phendimetrazine may decrease the hypotensive effect of guanethidine.

The least amount feasible should be prescribed or dispensed at one time in order to minimize the possibility of overdosage.

Carcinogenesis, Mutagenesis, Impairment of Fertility

Studies with phendimetrazine tartrate sustained release have not been performed to evaluate carcinogenic potential, mutagenic potential or effects on fertility.

Pregnancy

Phendimetrazine tartrate is contraindicated during pregnancy because weight loss offers no potential benefit to a pregnant woman and may result in fetal harm. A minimum weight gain, and no weight loss, is currently recommended for all pregnant women, including those who are already overweight or obese, due to obligatory weight gain that occurs in maternal tissues during pregnancy. Phendimetrazine tartrate, a phenylalkylamine sympathomimetic amine has pharmacological activity similar to amphetamines (see CLINICAL PHARMACOLOGY). Animal reproduction studies have not been conducted in phendimetrazine tartrate. If this drug is used during pregnancy, or if the patient becomes pregnant while taking this drug, the patient should be apprised of the potential hazard to a fetus.

Nursing Mothers

It is not known if phendimetrazine tartrate is excreted in human milk. Phendimetrazine tartrate, a phenylalkylamine sympathomimetic amine, has pharmacological activity similar to the amphetamines (see CLINICAL PHARMACOLOGY), and other amphetamines are present in human milk. Because of the potential for serious adverse reactions in nursing infants, a decision should be made whether to discontinue nursing or to discontinue the drug, taking into account the importance of the drug to the mother.

Drug Interactions

Monoamine Oxidase Inhibitors

Use of phendimetrazine tartrate is contraindicated during or within 14 days following the administration of monoamine oxidase inhibitors because of the risk of hypertensive crisis.

Alcohol

Concomitant use of alcohol with phendimetrazine tartrate may result in an adverse drug reaction.

Insulin and Oral Hypoglycemic Medications

Requirements may be altered.

Adrenergic Neuron Blocking Drugs

Phendimetrazine tartrate may decrease the hypotensive effect of adrenergic neuron blocking drugs.

Pediatric Use

Safety and effectiveness in pediatric patients have not been established. Because pediatric obesity is a chronic condition requiring long-term treatment, the use of phendimetrazine tartrate ER approved for short-term therapy, is not recommended in patients less than 17 years of age.

Renal Impairment

Phendimetrazine tartrate extended-release capsules were not studied in patients with renal impairment. As phendimetrazine tartrate is excreted in urine, exposure increases can be expected in patients with renal impairment. Use caution when administering phendimetrazine tartrate to patients with renal impairment.

Geriatric Use

In general, dose selection for an elderly patient should be cautious, usually starting at the low end of the dosing range, reflecting the greater frequency of decreased hepatic, renal, or cardiac function, and of concomitant disease or other drug therapy.

The major route of elimination is via the kidney where most of the drug and metabolites are excreted. The risk of toxic reactions to this drug may be greater in patients with impaired renal function. Because elderly patients are more likely to have decreased renal function, care should be taken in dose selection, and it may be useful to monitor renal function.

ADVERSE REACTIONS

The following adverse reactions are described, or described in greater detail, in other sections:

- Primary pulmonary hypertension (see WARNINGS)
- Valvular heart disease (see WARNINGS)
- Effect on the ability to engage in potentially hazardous tasks (see WARNINGS)
- Withdrawal effects following prolonged high dosage administration (see DRUG ABUSE AND DEPENDENCE)

The following adverse reactions to phendimetrazine have been identified:

Cardiovascular

Primary pulmonary hypertension and/or regurgitant cardiac valvular disease, palpitation, tachycardia, elevated blood pressure, ischemic events.

Central Nervous System

Overstimulation, restlessness, insomnia, agitation, flushing, tremor, sweating, dizziness, headache, psychotic state, blurring of vision.

Gastrointestinal

Dryness of the mouth, nausea, stomach pain, diarrhea, constipation.

Genitourinary

Urinary frequency, dysuria, changes in libido.

DRUG ABUSE AND DEPENDENCE

Controlled Substance

Phendimetrazine tartrate extended-release capsules are defined by the Drug Enforcement Administration as a Schedule III controlled substance.

Abuse

Phendimetrazine tartrate is related chemically and pharmacologically to the amphetamines. Amphetamines and related stimulant drugs have been extensively abused, and the possibility of abuse of phendimetrazine should be kept in mind when evaluating the desirability of including a drug as part of a weight reduction program.

Dependence

Abuse of amphetamines and related drugs may be associated with intense psychological dependence and severe social dysfunction. There are reports of patients who have increased the dosage to many times that recommended. Abrupt cessation following prolonged high dosage administration results in extreme fatigue and mental depression; changes are also noted on the sleep EEG. Manifestations of chronic intoxication with anorectic drugs include severe dermatoses, marked insomnia, irritability, hyperactivity and personality changes. The most severe manifestation of chronic intoxications is psychosis, often clinically indistinguishable from schizophrenia.

OVERDOSAGE

The least amount feasible should be prescribed or dispensed at one time in order to minimize the possibility of overdosage.

Acute Overdosage

Acute overdosage with phendimetrazine tartrate may manifest itself by the following signs and symptoms: unusual restlessness, confusion, belligerence, hallucinations, and panic states. Fatigue and depression usually follow the central stimulation. Cardiovascular effects include tachycardia, arrhythmias, hypertension, or hypotension and circulatory collapse. Gastrointestinal symptoms include nausea, vomiting, diarrhea, and abdominal cramps. Poisoning may result in convulsions, coma, and death.

The management of acute overdosage is largely symptomatic. It includes lavage and sedation with a barbiturate. If hypertension is marked, the use of a nitrate or rapid-acting alpha receptor-blocking agent should be considered. Experience with hemodialysis or peritoneal dialysis is inadequate to permit recommendations for its use.

Chronic Intoxication

Manifestations of chronic intoxication with anorectic drugs include severe dermatoses, marked insomnia, irritability, hyperactivity and personality changes. The most severe manifestation of chronic intoxications is psychosis, often clinically indistinguishable from schizophrenia. See DRUG ABUSE AND DEPENDENCE.

DOSAGE AND ADMINISTRATION

Since the product is an extended-release dosage form, limit to one extended-release capsule (105 mg phendimetrazine tartrate) in the morning (30 to 60 minutes before morning meal).

Each extended-release capsule contains 105 mg phendimetrazine tartrate in a Brown/Clear capsule imprinted E 5254.

HOW SUPPLIED

NDC 72989-409-30 - bottle of 30 capsules

NDC 72989-409-11 - bottle of 1,000 capsules

Store at 20° to 25°C (68° to 77°F) [see USP Controlled Room Temperature]. Protect from moisture.

DISPENSE IN A TIGHT CONTAINER AS DEFINED IN THE USP.

To report SUSPECTED ADVERSE REACTIONS, contact Acertis Pharmaceuticals, LLC at 1-888-848-3593 or FDA at 1-800-FDA-1088 or www.fda.gov/medwatch.

Distributed by

Acertis Pharmaceuticals, LLC

Raleigh, NC 27601

Rev. 05/2025

MF5254REV05/25

OE2820

PACKAGE/LABEL PRINCIPAL DISPLAY PANEL - 30-count Bottle Label

NDC 72989-409-30

Phendimetrazine
Tartrate
Extended-Release
Capsules CIII

105 mg
Rx Only
30 Capsules

acertis™
PHARMACEUTICALS